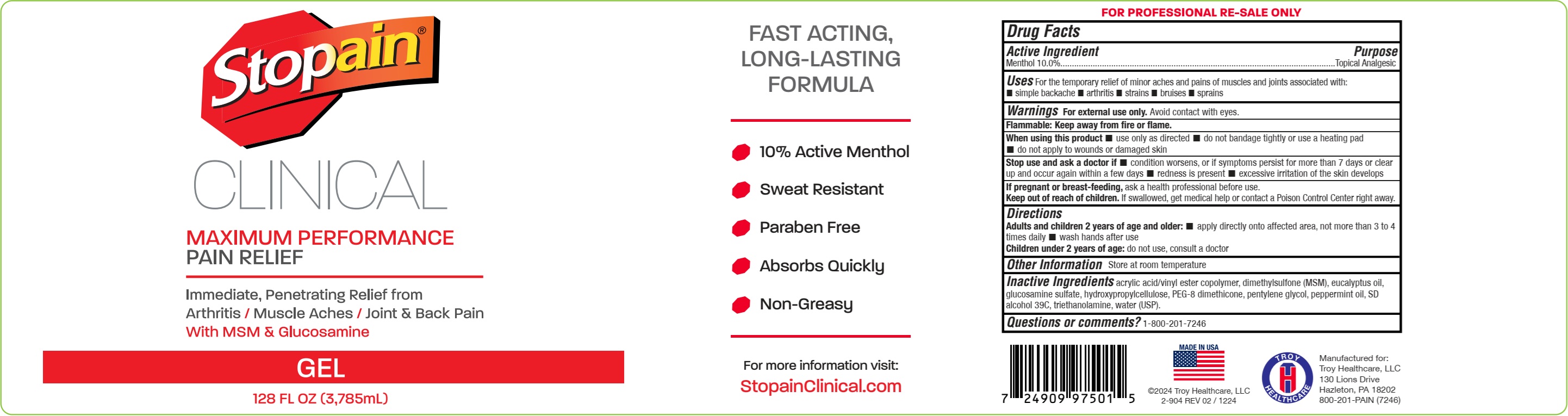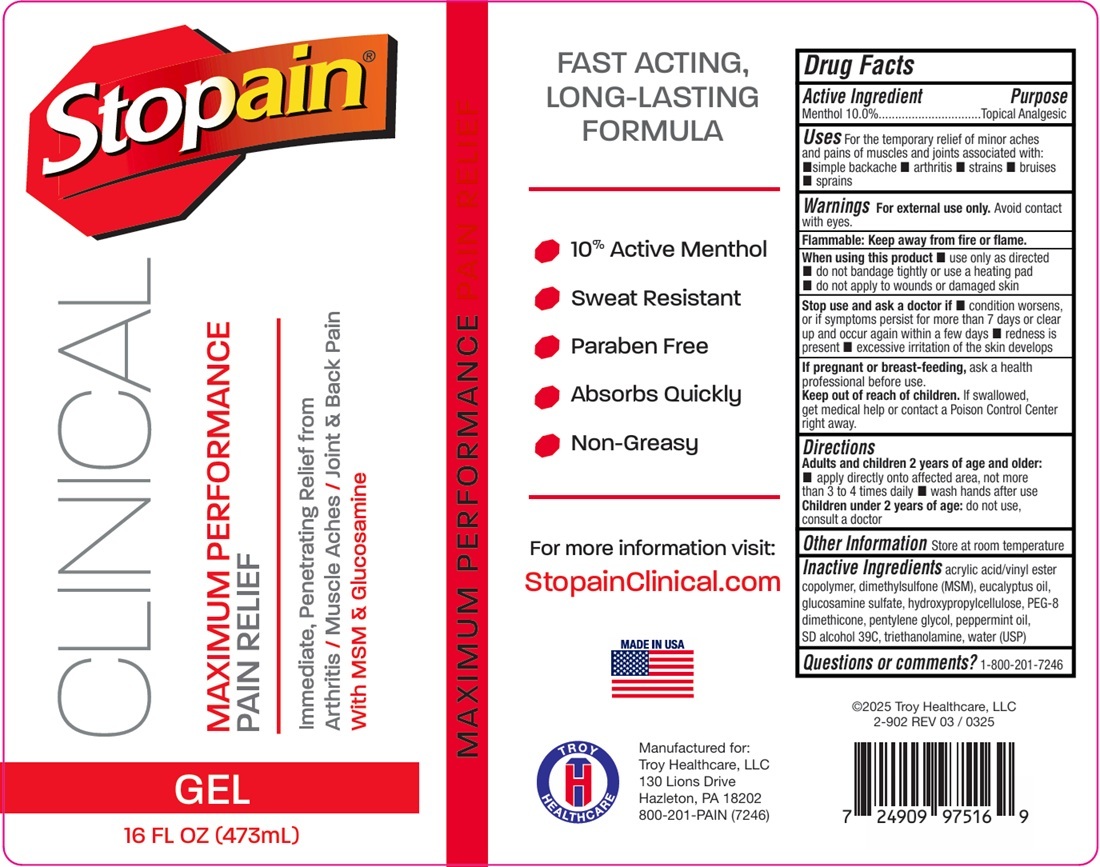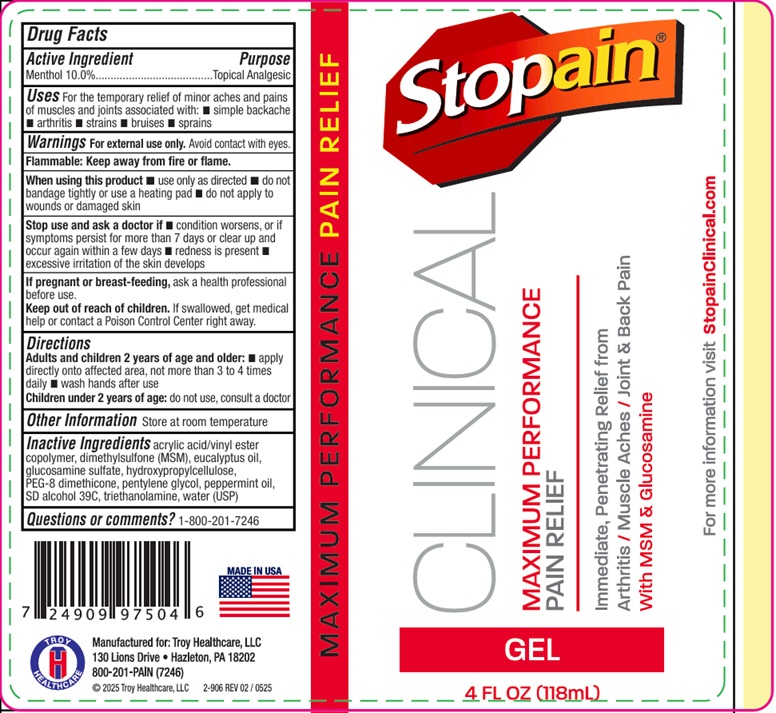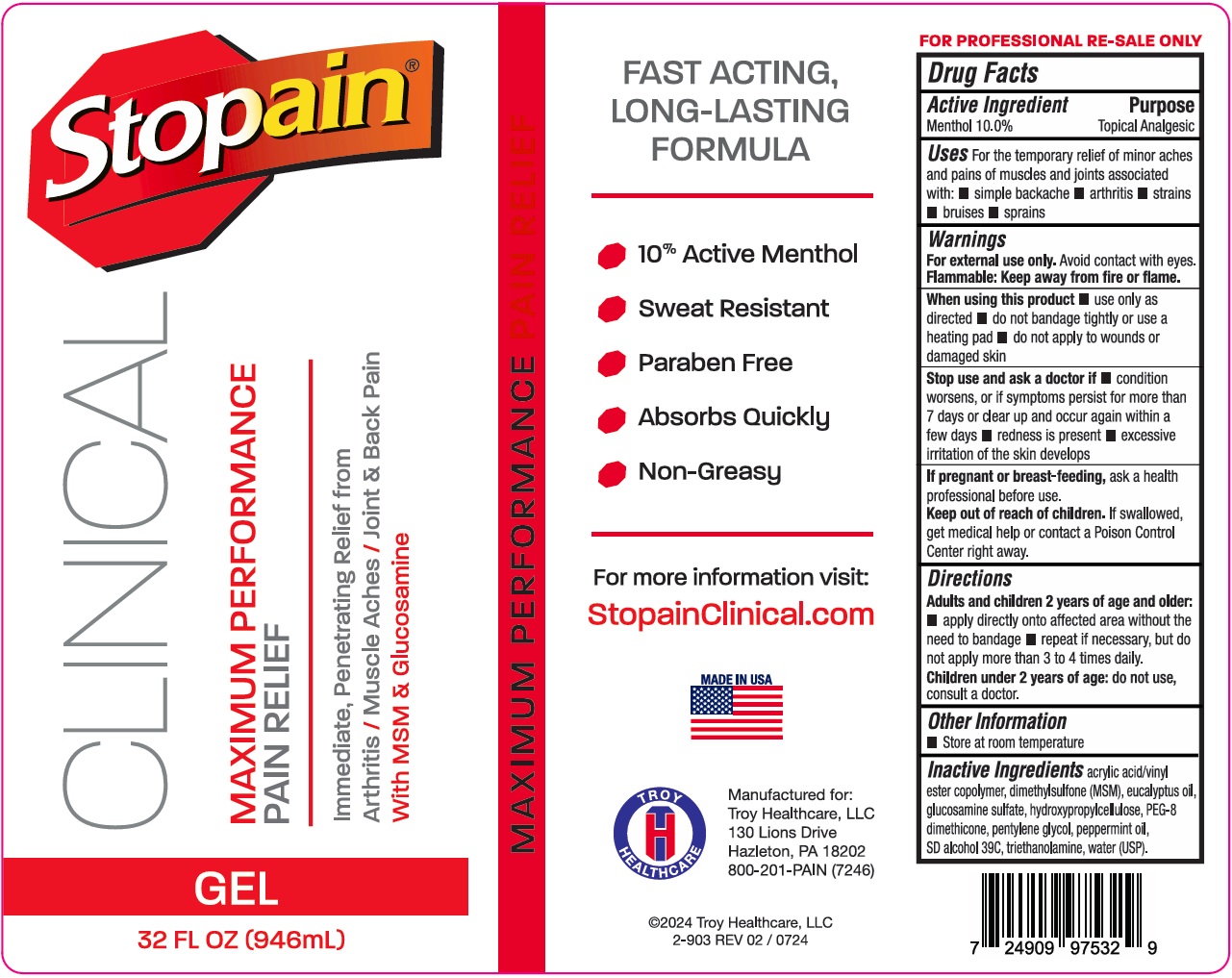 DRUG LABEL: Stopain Clinical
NDC: 63936-9750 | Form: GEL
Manufacturer: Troy Manufacturing, Inc.
Category: otc | Type: HUMAN OTC DRUG LABEL
Date: 20250904

ACTIVE INGREDIENTS: MENTHOL, UNSPECIFIED FORM 100 mg/1 mL
INACTIVE INGREDIENTS: ACRYLIC ACID; DIMETHYL SULFONE; EUCALYPTUS OIL; GLUCOSAMINE SULFATE; HYDROXYPROPYL CELLULOSE, UNSPECIFIED; PEG-8 DIMETHICONE; PENTYLENE GLYCOL; PEPPERMINT OIL; TROLAMINE; WATER

Stopain Clinical Gel

Active Ingredient

Menthol 10.0%

Purpose

Topical Analgesic

Uses

For the temporary relief of minor aches and pains of muscles and joints associated with:

- simple backache
- arthritis
- strains
- bruises
- sprains

Warnings

Avoid contact with eyes. For external use only.

Flammable: Keep away from fire or flame.

When using this product

- use only as directed
- do not bandage tightly or use a heating pad
- do not apply to wounds or damaged skin

Stop use and ask a doctor if

- condition worsens, or if symptoms persist for more than 7 days or clear up and occur again within a few days
- redness is present
- excessive irritation of the skin develops

If pregnant or breast-feeding,

ask a health professional before use.

Keep out of reach of children.

If swallowed, get medical help or contact a Poison Control Center right away.

Directions

Adults and children over 12 years:

ask a doctor. Children 12 years or younger:

- apply directly onto affected area without the need to bandage
- repeat if necessary, but do not apply more than 4 times daily.

Other Information

- Store at room temperature

Inactive Ingredients

acrylic acid/vinyl ester copolymer, dimethylsulfone (MSM), eucalyptus oil, glucosamine sulfate, hydroxypropylcellulose, SD alcohol 39C, PEG-8 dimethicone, pentylene glycol, peppermint oil, triethanolamine, water (USP).